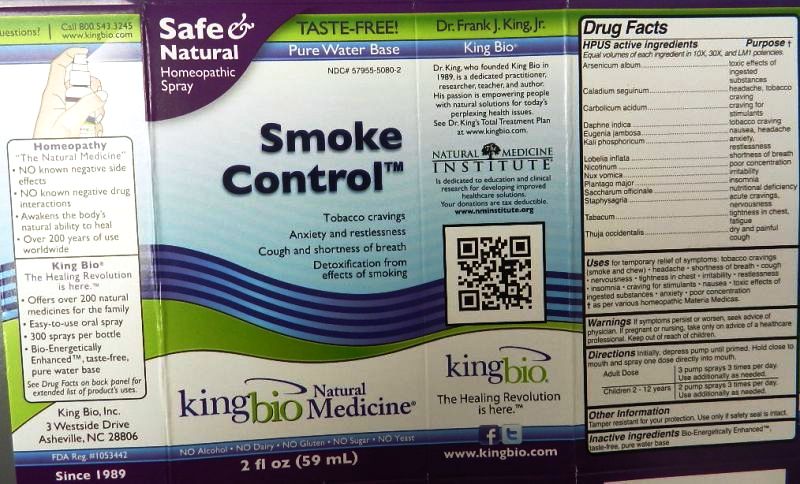 DRUG LABEL: Smoke Control
NDC: 57955-5080 | Form: LIQUID
Manufacturer: King Bio Inc.
Category: homeopathic | Type: HUMAN OTC DRUG LABEL
Date: 20111021

ACTIVE INGREDIENTS: ARSENIC TRIOXIDE 10 [hp_X]/59 mL; DIEFFENBACHIA SEGUINE 10 [hp_X]/59 mL; PHENOL 10 [hp_X]/59 mL; DAPHNE ODORA BARK 10 [hp_X]/59 mL; SYZYGIUM JAMBOS SEED 10 [hp_X]/59 mL; POTASSIUM PHOSPHATE, DIBASIC 10 [hp_X]/59 mL; LOBELIA INFLATA 10 [hp_X]/59 mL; NICOTINE 10 [hp_X]/59 mL; STRYCHNOS NUX-VOMICA SEED 10 [hp_X]/59 mL; PLANTAGO MAJOR 10 [hp_X]/59 mL; SUCROSE 10 [hp_X]/59 mL; DELPHINIUM STAPHISAGRIA SEED 10 [hp_X]/59 mL; TOBACCO LEAF 10 [hp_X]/59 mL; THUJA OCCIDENTALIS LEAFY TWIG 10 [hp_X]/59 mL
INACTIVE INGREDIENTS: WATER

Smoke Control

Active Ingredient

HPUS active ingredients

Equal volumes of each ingredient in 10X, 30X, and LM1 potencies.

Arsenicum album

Caladium seguinum

Carbolicum acidum

Daphne indica

Eugenia jambosa

Kali phosphoricum

Lobelia inflata

Nicotinum

Nux vomica

Plantago major

Saccharum officinale

Staphysagria

Tabacum

Thuja occidentalis

Reference image of smoke.jpg

Inactive Ingredient

Inactive ingredients

Bio-Energetically Enhanced taste-free, pure water base

Reference image of smoke.jpg

Dosage and Administration

Directions Initially, depress pump until primed. Hold close to mouth and spray one dose directly into mouth.

Adult Dose- 3 pump sprays 3 times per day. Use additionally as needed.

Children 2-12 years- 2 pump sprays 3 times per day. Use additionally as needed.

Reference image of smoke.jpg

Purpose

HPUS active ingredients Purpose

Equal volumes of each ingredient in 10X, 30X, and LM1 potencies.

Arsenicum album...........................................toxic effects of ingested substances

Caladium seguinum........................................headache, tobacco craving

Carbolicum acidum........................................craving for stimulants

Daphne indica................................................tobacco craving

Eugenia jambosa...........................................nausea, headache

Kali phosphoricum.........................................anxiety, restlessness

Lobelia inflata................................................shortness of breath

Nicotinum.....................................................poor concentration

Nux vomica..................................................irritability

Plantago major.............................................insomnia

Saccharum officinale...................................nutritional deficiency

Staphysagria...............................................acute cravings, nervousness

Tabacum.....................................................tightness in chest, fatigue

Thuja occidentalis........................................dry and painful cough

Reference image of smoke.jpg

Warnings

If symptoms persist or worsen, seek advice of physician. If pregnant or nursing, take only on advice of a healthcare professional. Keep out of reach of children.

Other information

Tamper resistant for your protection. Use only if safety seal is intact.

Reference image smoke.jpg

Keep Out Of Reach Of Children

Reference image smoke.jpg

Indications and Usage

Uses for temporary relief of symptoms:

- tobacco cravings (smoke and chew)
- headache
- shortness of breath
- cough
- nervousness
- tightness in chest
- irritability
- restlessness
- insomnia
- craving for stimulants
- nausea
- toxic effects of ingested substances
- anxiety
- poor concentration

as per various homeopathic Materia Medicas
Reference image smoke.jpg

PACKAGE LABEL

King Bio Inc.
3 Westside Drive
Asheville, NC 28806
www.kingbio.com

Reference image smoke.jpg